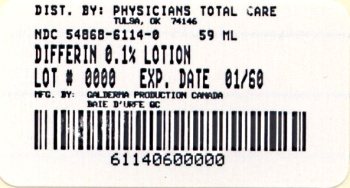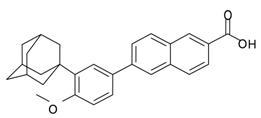 DRUG LABEL: Differin 
NDC: 54868-6114 | Form: LOTION
Manufacturer: Physicians Total Care, Inc.
Category: prescription | Type: HUMAN PRESCRIPTION DRUG LABEL
Date: 20120307

ACTIVE INGREDIENTS: Adapalene 1 mg/1 g
INACTIVE INGREDIENTS: Carbomer Homopolymer Type A; Edetate Disodium; Medium-chain Triglycerides; Methylparaben; Phenoxyethanol; Poloxamer 124; Propylene Glycol; Propylparaben; Sodium Hydroxide; Stearyl Alcohol; Water

HIGHLIGHTS OF PRESCRIBING INFORMATION

These highlights do not include all the information needed to use DIFFERIN safely and effectively. See full prescribing information for DIFFERIN Lotion.
DIFFERIN® (adapalene) Lotion 0.1%
For topical use only
Initial U.S. Approval: 1996

1 INDICATIONS AND USAGE

DIFFERIN Lotion is a retinoid product indicated for the topical treatment of acne vulgaris in patients 12 years and older. (1)

2 DOSAGE AND ADMINISTRATION

Apply a thin film of DIFFERIN Lotion to the entire face and other affected areas of the skin once daily, after washing gently with a mild soapless cleanser. Dispense a nickel size amount of DIFFERIN Lotion (3-4 actuations of the pump) to cover the entire face. Avoid application to the areas of skin around eyes, lips and mucous membranes. (2)

DIFFERIN Lotion is for topical use only and not for oral, ophthalmic, or intravaginal use. (2)

3 DOSAGE FORMS AND STRENGTHS

Each gram of the lotion contains 1 mg (0.1%) adapalene in an oil-in-water emulsion. (3)

4 CONTRAINDICATIONS

None. (4)

5 WARNINGS AND PRECAUTIONS

Ultraviolet Light and Environmental Exposure: Avoid exposure to sunlight and sunlamps. Wear sunscreen when sun exposure cannot be avoided. (5.1).

Erythema, scaling, dryness, and stinging/ burning may occur with use of DIFFERIN Lotion. (5.2)

6 ADVERSE REACTIONS

Dry skin of mild to moderate severity was the most frequently reported (≥ 1%) treatment related adverse vent. Erythema, scaling, dryness, burning/stinging were also seen during treatment. (6)

To report SUSPECTED ADVERSE REACTIONS, contact Galderma Laboratories, L.P. at 1-866-735-4137 or FDA at 1-800-FDA-1088 or www.fda.gov/medwatch

7 DRUG INTERACTIONS

Concomitant use of topical products with a strong drying effect can increase skin irritation. Use with caution, especially in using preparations containing sulfur, resorcinol, or salicylic acid in combination with DIFFERIN Lotion. (7.1)

FULL PRESCRIBING INFORMATION

1 INDICATIONS AND USAGE

DIFFERIN Lotion is indicated for the topical treatment of acne vulgaris in patients 12 years and older.

2 DOSAGE AND ADMINISTRATION

Apply a thin film of DIFFERIN Lotion to the entire face and other affected areas of the skin once daily, after washing gently with a mild soapless cleanser. Dispense a nickel size amount of DIFFERIN Lotion (3-4 actuations of the pump) to cover the entire face. Avoid application to the areas of skin around eyes, lips and mucous membranes.

DIFFERIN Lotion is for topical use only and not for oral, ophthalmic, or intravaginal use.

3 DOSAGE FORMS AND STRENGTHS

Each gram of the lotion contains 1 mg (0.1%) adapalene in an oil-in-water emulsion.

4 CONTRAINDICATIONS

None.

5 WARNINGS AND PRECAUTIONS

5.1 Ultraviolet Light and Environmental Exposure

Exposure to sunlight, including sunlamps, should be avoided during the use of DIFFERIN Lotion. Patients with high levels of sun exposure and those with inherent sensitivity to sun should be warned to exercise caution. Use of sunscreen products and protective apparel (e.g. hat) are recommended when exposure cannot be avoided. Weather extremes, such as wind or cold, may be irritating to patients under treatment with DIFFERIN Lotion.

5.2 Local Cutaneous Reactions

Signs and symptoms of local skin irritation (such as erythema, scaling, dryness, stinging/burning) may be experienced with use of DIFFERIN Lotion. These are most likely to occur during the first 2 weeks of treatment, are mostly mild to moderate in severity, and usually lessen with continued use of DIFFERIN Lotion. Depending upon the severity of these side effects, patients should be instructed to use a moisturizer, reduce the frequency of the application of DIFFERIN Lotion 0.1%, or discontinue use.

DIFFERIN Lotion should not be applied to cuts, abrasions, eczematous or sunburned skin. As with other retinoids, use of “waxing” as a depilatory method should be avoided on skin treated with DIFFERIN Lotion.

Avoid concomitant use of other potentially irritating topical products (abrasive soaps and cleansers, soaps and cosmetics that have strong skin-drying effect and products with high concentrations of alcohol, astringents, spices, or limes).

6 ADVERSE REACTIONS

6.1 Clinical Studies Experience

Because clinical studies are conducted under widely varying conditions, adverse reaction rates observed in the clinical studies of a drug cannot be directly compared to rates in the clinical studies of another drug and may not reflect the rates observed in practice.

A total of 2141 subjects with acne vulgaris, 12 years and older, were treated once daily for 12 weeks. Of these, 1068 were exposed to DIFFERIN Lotion during the clinical trials. A total of 1057 subjects completed at least one post treatment evaluation.

Related adverse reactions that were reported in at least 1% of patients treated with DIFFERIN Lotion or with the Vehicle Lotion are presented in Table 1.

The majority of cases was transient, mild to moderate in severity and was managed with moisturizers.

Table 1: Adverse Reactions Reported in Clinical Trials by At Least 1% of Patients
System Term | Organ | Class/Preferred | Adapalene Lotion 0.1% N = 1068 | Vehicle Lotion N = 1073
Subjects with Related AR(s) |  |  | 10.2% | 4.6%
Dry Skin |  |  | 7.7% | 3.0%
Skin Irriitation |  |  | 1.5% | 0.7%
Skin burning/skin discomfort |  |  | 0.9% | 0.0%
Sunburn |  |  | 0.6% | 0.6%

Local tolerability evaluations, presented in Table 2, were conducted at each study visit in clinical trials. Erythema, scaling, dryness, burning/stinging were assessed:

Table 2: Incidence of Local Cutaneous Irritation, for Subjects Whose Irritation Score was Higher than at Baseline, in Controlled Clinical Studies Adverse Reactions (DIFFERIN Lotion Group N = 1057)
Combined Study 1 and Study 2 | Maximum Severity During Treatment (N = 1057) |  |  | Week 12 Treatment Severity (N = 950)
Local Cutaneous Irritation (skin irritation) | Mild | Moderate | Severe | Mild | Moderate | Severe
Erythema | 21.8% | 8.0% | 0.2% | 7.9% | 2.6% | 0.2%
Scaling | 25.3% | 6.5% | 0.1% | 5.3% | 1.1% | 0
Dryness | 36.1% | 7.3% | 0.3% | 7.6% | 2.0% | 0
Stinging/burning | 22.1% | 7.0% | 0.9% | 4.6% | 1.0% | 0.4%

Local tolerability scores for erythema, scaling, dryness, burning/stinging rose during the first two weeks of treatment and generally decreased thereafter.

7 DRUG INTERACTIONS

7.1 Concomitant Topical Medications

Concomitant topical acne therapy should be used with caution because a possible cumulative irritancy effect may occur, especially with the use of peeling, desquamating, or abrasive agents. Caution should be exercised in using preparation containing sulfur, resorcinol or salicylic acid in combination with DIFFERIN Lotion.

No formal drug-drug interaction studies were conducted with DIFFERIN Lotion.

8 USE IN SPECIFIC POPULATIONS

8.1 Pregnancy

Pregnancy Category C. There are no well-controlled trials in pregnant women treated with DIFFERIN Lotion. Therefore, DIFFERIN Lotion should be used during pregnancy only if the potential benefit justifies the potential risk to the fetus. Animal reproduction studies have not been conducted with DIFFERIN Lotion. Furthermore, such studies are not always predictive of human response.

Human Data

In clinical trials involving DIFFERIN Lotion, 0.1% in the treatment of acne vulgaris, women of childbearing potential initiated treatment only after a negative pregnancy test. Two women became pregnant while using DIFFERIN Lotion, 0.1%. One patient delivered a healthy full term baby and the other patient electively terminated her pregnancy.

Animal Data

No teratogenic effects were observed in rats treated with oral doses of 0.15 to 5.0 mg adapalene/kg/day, up to 25 times (mg/m2/day) the maximum recommended human dose (MRHD) of 2 grams of DIFFERIN Lotion. However, teratogenic changes were observed in rats and rabbits when treated with oral doses of ≥ 25 mg adapalene/kg/day representing 123 and 246 times MRHD, respectively. Findings included cleft palate, microphthalmia, encephalocele and skeletal abnormalities in rats; and umbilical hernia, exophthalmos and kidney and skeletal abnormalities in rabbits.

Dermal teratology studies conducted in rats and rabbits at doses of 0.6-6.0 mg adapalene/kg/day [25-59 times (mg/m^2) the MRHD] exhibited no fetotoxicity and only minimal increases in supernumerary ribs in both species and delayed ossification in rabbits.

Systemic exposure (AUC 0-24h) to adapalene at topical doses (6.0 mg/kg/day) in rats represented 101 times the exposure to adapalene in patients with acne treated with DIFFERIN Lotion applied to the face, chest and back (2 grams applied to 1000 cm² of acne-involved skin).

8.3 Nursing Mothers

It is not known whether adapalene is excreted in human milk following use of DIFFERIN Lotion. Because many drugs are excreted in human milk, caution should be exercised when DIFFERIN Lotion is administered to a nursing woman.

8.4 Pediatric Use

Safety and effectiveness of DIFFERIN Lotion in pediatric patients under the age of 12 have not been established.

8.5 Geriatric Use

Clinical studies of DIFFERIN Lotion did not include sufficient numbers of subjects aged 65 and over to determine whether they respond differently from younger subjects.

11 DESCRIPTION

DIFFERIN (adapalene) Lotion, 0.1% for topical use, is an adapalene-based product.

Adapalene is a naphthoic acid derivative with retinoid-like properties. The chemical name for adapalene is (6-[3-(1-adamantyl)-4-meghoxyphenyl]-2-naphthoic acid). Adapalene has the following structural formula:

Adapalene:

Molecular formula: C28H28O3 Molecular weight: 412.5

DIFFERIN Lotion contains the following inactive ingredients: carbomer 941, disodium edetate, medium chain triglycerides, methylparaben, phenoxyethanol, poloxamer 124, polyoxyl-6-polyoxyl-32 palmitostearate, PPG-12/SMDI copolymer, propylene glycol, propylparaben, sodium hydroxide, stearyl alcohol, and purified water.

12 CLINICAL PHARMACOLOGY

12.1 Mechanism of Action

Adapalene binds to specific retinoic acid nuclear receptors but does not bind to cytosolic receptor protein. Biochemical and pharmacological profile studies have demonstrated that adapalene is a modulator of cellular differentiation, keratinization and inflammatory processes. However, the significance of these findings with regard to the mechanism of action of adapalene for the treatment of acne is unknown.

12.2 Pharmacodynamics

Pharmacodynamics of DIFFERIN Lotion is unknown.

12.3 Pharmacokinetics

Systemic exposure of adapalene following a topical application of DIFFERIN Lotion was studied in one clinical study. Fourteen subjects at 18-29 years of age with severe acne were treated with 2 g of DIFFERIN Lotion once daily for 30 days to approximately 1000 cm^2 of acne involved skin. Serial plasma samples were collected for 24 or 72 hours following application on days 1, 15 and 30. All plasma concentrations for 12 out of 14 patients were below the limit of quantification (LOQ=0.1 ng/mL). One patient had one sample above LOQ at day 30 and the other patient had four plasma samples above LOQ on both days 1 and 15, which ranged from 0.102 and 0.131 ng/mL. Due to the limited number of available data points, PK analysis was not undertaken.

13 NONCLINICAL TOXICOLOGY

13.1 Carcinogenesis, Mutagenesis, Impairment of Fertility

No carcinogenicity, mutagenicity and impairment of fertility studies were conducted with DIFFERIN Lotion.

Carcinogenicity studies with adapalene have been conducted in mice at topical doses of 0.4, 1.3, and 4.0 mg/kg/day (1.2, 3.9, and 12 mg/m^2/day), and in rats at oral doses of 0.15, 0.5, and 1.5 mg/kg/day (0.9, 3.0, and 9.0 mg/m^2/day). In terms of body surface area, the highest dose levels are 9.8 (mice) and 7.4 times (rats) the MRHD of 2 grams of DIFFERIN Lotion. In the rat study, an increased incidence of benign and malignant pheochromocytomas in the adrenal medulla of male rats was observed.

No photocarcinogenicity studies were conducted with adapalene. However, animal studies have shown an increased tumorigenic risk with the use of pharmacologically similar drugs (e.g. retinoids) when exposed to UV irradiation in the laboratory or sunlight. Although the significance of these findings to humans is not clear, patients should be advised to avoid or minimize exposure to either sunlight or artificial irradiation sources.

Adapalene did not exhibit mutagenic or genotoxic effects in vitro (Ames test, Chinese hamster ovary cell assay, mouse lymphoma TK assay) or in vivo (mouse micronucleus test).

In rat oral studies, 20 mg adapalene/kg/day (120 mg/m^2/day; 98 times the MRHD based on mg/m^2/day comparison) did not affect the reproductive performance and fertility of F0 males and females, or growth, development and reproductive function of F1 offspring.

14 CLINICAL STUDIES

The safety and efficacy of DIFFERIN Lotion applied once daily for the treatment of acne vulgaris were assessed in two 12-week, multicenter, controlled clinical studies of similar design, comparing DIFFERIN Lotion to the Lotion vehicle in acne subjects.

In Study 1, 1075 subjects were randomized to DIFFERIN Lotion or vehicle. The median age of these subjects was 16.7 years old and 53.1% were females. At baseline subjects had between 20 to 50 inflammatory lesions and 30 to 100 non-inflammatory lesions. The majority of subjects (91.0%) had a baseline IGA score of ‘Moderate’.

In Study 2, 1066 subjects were randomized to DIFFERIN Lotion or vehicle. The median age of subjects was 16.7 years old and 53.7% were females. At baseline subjects had the same inclusion criteria as in Study 1 and 95.7% of subjects had a baseline IGA score of ‘Moderate’.

The outcome of the two studies is presented in Table 3.

Table 3: Clinical Study Primary Efficacy Results at Week 12
Study 1
 | DIFFERIN Lotion (N = 533) | Vehicle Lotion (N = 542)
IGA Success | 140 (26.3%) | 94 (17.3%)
Total Lesions: Mean Absolute (Percent) Change | 37.9 (51.5%) | 26.7 (37.1%)
Inflammatory Lesions: Mean Absolute (Percent) Change | 14.7 (54.9%) | 10.6 (40.3%)
Non-inflammatory Lesions: Mean Absolute (Percent) Change | 23.2 (49.6%) | 16.1 (35.7%)

Study 2
 | DIFFERIN Lotion (N = 535) | Vehicle Lotion (N = 531)
IGA Success | 129 (24.1%) | 87 (16.4%)
Total Lesions: Mean Absolute (Percent) Change | 32.4 (44.6%) | 23.4 (32.8%)
Inflammatory Lesions: Mean Absolute (Percent) Change | 12.7 (46.0%) | 10.2 (36.9%)
Non-inflammatory Lesions: Mean Absolute (Percent) Change | 19.6 (43.1%) | 13.1 (30.2%)

16 HOW SUPPLIED/STORAGE AND HANDLING

DIFFERIN (adapalene) Lotion, 0.1%, is packaged in a 2 oz (59 mL) bottle which is equipped with a Lotion dispensing pump.

The DIFFERIN Lotion is supplied as follows:

2 oz bottle pump (59 mL) NDC 54868-6114-0

Storage and handling

- Store at controlled room temperature, 20 - 25°C (68 - 77°F); excursions permitted to 15 – 30°C (59 – 86°F).
- Do not freeze.
- Do not refrigerate.
- Protect from light.
- Keep out of reach of children.
- Keep away from heat.
- Keep bottle tightly closed.

17 PATIENT COUNSELING INFORMATION

- Apply a thin film of DIFFERIN Lotion to the affected areas of the skin once daily, after washing gently with a mild soapless cleanser. Dispense a nickel size amount of DIFFERIN Lotion (3-4 actuations of the pump) to cover the entire face. Avoid application to the areas of skin around eyes, lips and mucous membranes. DIFFERIN Lotion may cause irritation such as erythema, scaling, dryness, stinging or burning.
- Advise patients to cleanse the area to be treated with a mild or soapless cleanser; pat dry. Apply DIFFERIN Lotion to the entire face or other acne affected areas as a thin layer, avoiding the eyes, lips and mucous membranes.
- Exposure of the eye to this medication may result in reactions such as swelling, conjunctivitis and eye irritation.
- Patients should be advised not to use more than the recommended amount and not to apply more than once daily as this will not produce faster results, but may increase irritation.
- Advise patients to minimize exposure to sunlight including sunlamps. Recommend the use of sunscreen products and protective apparel (e.g., hat) when exposure cannot be avoided.
- Moisturizers may be used if necessary; however, products containing alpha hydroxy or glycolic acids should be avoided.
- This medication should not be applied to cuts, abrasions, eczematous, or sunburned skin.
- Wax depilation should not be performed on treated skin due to the potential for skin erosions.
- This product is for external use only.

Marketed by:
GALDERMA LABORATORIES, L.P., Fort Worth, Texas 76177 USA
Manufactured by:
Galderma Production Canada Inc., Baie d’Urfé, QC, H9X 3S4 Canada
Made in Canada.
GALDERMA is a registered trademark.
P51503-0

Additional barcode labeling by:
Physicians Total Care, Inc.
Tulsa, Oklahoma 74146

PACKAGE LABEL

Rx Only

NDC 54868-6114-0

Differin®
(adapalene) Lotion 0.1%

For External
Use Only

2 FL OZ
(59 mL)

For external use only.

Not for ophthalmic oral or intravaginal use.

Usual dosage: Apply a thin film on the entire face and other affected areas of the skin once daily. See package insert for complete prescribing information.

Each gram contains: adapalene 1 mg (0.1%) in an aqueous based lotion consisting of the following inactive ingredients:
carbomer 941, disodium edetate, medium chain triglycerides, methylparaben, phenoxyethanol, poloxamer 124, polyoxyl-6-polyoxyl-32 palmitostearate, PPG-12/SMDI copolymer, propylene glycol, propylparaben, sodium hydroxide, stearyl alcohol, and purified water.

Storage: Store at controlled room temperature 68° - 77°F (20° - 25°C) with excursions permitted between 59° - 86°F (15° - 30°C). Do not freeze or refrigerate.